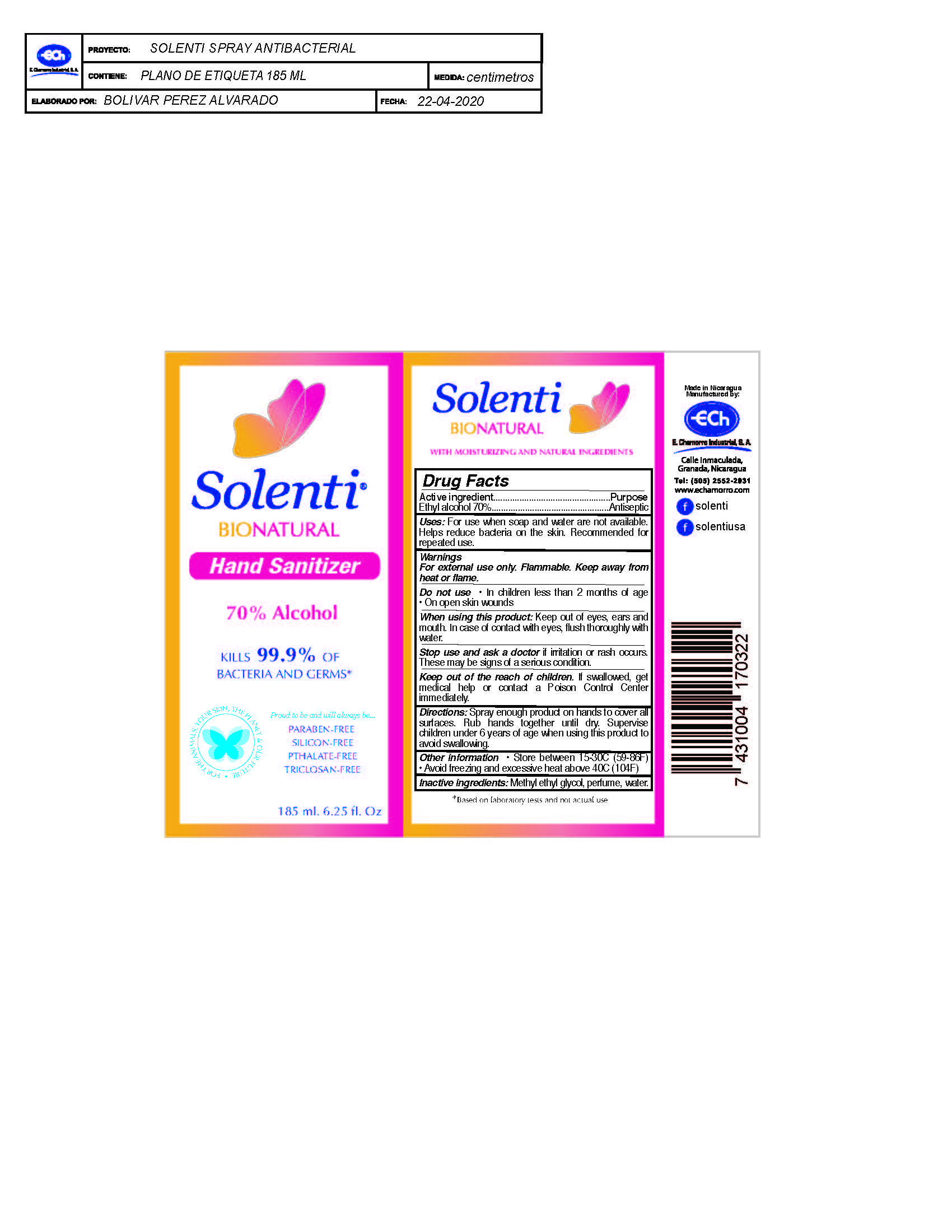 DRUG LABEL: Solenti BioNatural Hand Sanitizer
NDC: 75794-100 | Form: SPRAY
Manufacturer: E. Chamorro Industrial, S.A.
Category: otc | Type: HUMAN OTC DRUG LABEL
Date: 20210708

ACTIVE INGREDIENTS: ALCOHOL 42 mL/60 mL
INACTIVE INGREDIENTS: DIETHYLENE GLYCOL; WATER

Solenti BioNatural Hand Sanitizer

Active Ingredient

Ethyl Alcohol 70%

Purpose

Antiseptic

Uses

For use when soap and water are not available. Helps reduce bacteria on the skin. Recommended for repeated use.

Warnings

For External Use only. Flammable. Keep away from heat or flame

Do not Use

-In children less than 2 months of age- On open skin wounds

When using this product

Keep out of eyes, ears, and mouth. In case of contact with eyes, flush thoroughly with water.

Stop use and ask a doctor if

Irritation or rash occurs. These may be signs of a serious condition.

Keep out of reach of children

If swallowed, get medical help or contact a Poison Control Center immediately.

Directions

-Spray enough product on hands to cover all surfaces. Rub hands together until dry. -Supervise children under 6 years of age when using this product to avoid swallowing.

Other Information

Store between 15-30C (59-86F). -Avoid freezing and excessive above 40C (104F)

Inactive Ingredients

Methylethylglycol, perfume, water